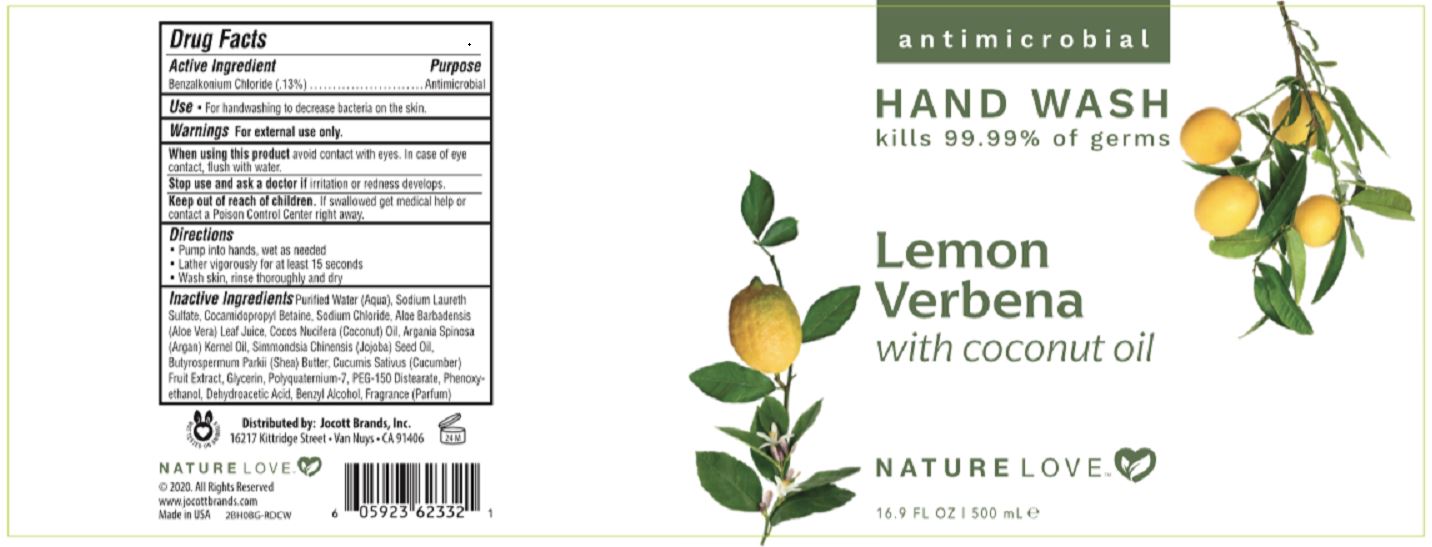 DRUG LABEL: NATURE LOVE ANTIMICROBIAL HAND WASH
NDC: 78902-208 | Form: SOAP
Manufacturer: Jocott Brands, Inc.
Category: otc | Type: HUMAN OTC DRUG LABEL
Date: 20201109

ACTIVE INGREDIENTS: BENZALKONIUM CHLORIDE 0.13 g/100 mL
INACTIVE INGREDIENTS: WATER; SODIUM LAURETH SULFATE; COCAMIDOPROPYL BETAINE; SODIUM CHLORIDE; ALOE VERA LEAF; COCONUT OIL; ARGAN OIL; JOJOBA OIL; SHEA BUTTER; CUCUMBER; GLYCERIN; POLYQUATERNIUM-7 (70/30 ACRYLAMIDE/DADMAC; 1600 KD); PEG-150 DISTEARATE; PHENOXYETHANOL; DEHYDROACETIC ACID; BENZYL ALCOHOL

NATURE LOVE ANTIMICROBIAL HAND WASH - LEMON VERBENA with coconut oil - BKC 0.13%

ACTIVE INGREDIENT

BENZALKONIUM CHLORIDE (0.13%0

PURPOSE

ANTIMICROBIAL

USE

- FOR HAND WASHING TO DECREASE BACTERIA ON THE SKIN.

WARNINGS

FOR EXTERNAL USE ONLY.

WHEN USING THIS PRODUCT AVOID CONTACT WITH EYES. IN CASE OF EYE CONTACT, FLUSH WITH WATER.

STOP USE AND ASK A DOCTOR IF IRRITATION OR REDNESS DEVELOPS.

KEEP OUT OF REACH OF CHILDREN. IF SWALLOWED GET MEDICAL HELP OR CONTACT A POISON CONTROL CENTER RIGHT AWAY.

DIRECTIONS

- PUMP INTO HANDS, WET AS NEEDED.
- LATHER VIGOUROUSLY FOR AT LEAST 15 SECONDS.
- WASH SKIN, RINSE THOROUGHLY AND DRY.

INACTIVE INGREDIENTS

Purified Water (Aqua), Sodium Laureth SUlfate, Cocamidopropyl Betaine, Sodium Chloride, Aloe Barbadensis (Aloe Vera) Leaf Juice, Cocos Nucifera (Coconut) Oil, Argania Spinosa (Argan) Kernel Oil, Simmondsia Chinensis (Jojoba) Seed Oil, Butyrospermum Parkii (Shea) Butter, Cucumis Sativus (Cucumber) Fruit Extract, Glycerin, Polyquaternium-7, PEG-150 Distearate, Phenoxyethanol, Dehydroacetic Acid, Benzyl Alcohol, Fragrance (Parfum)